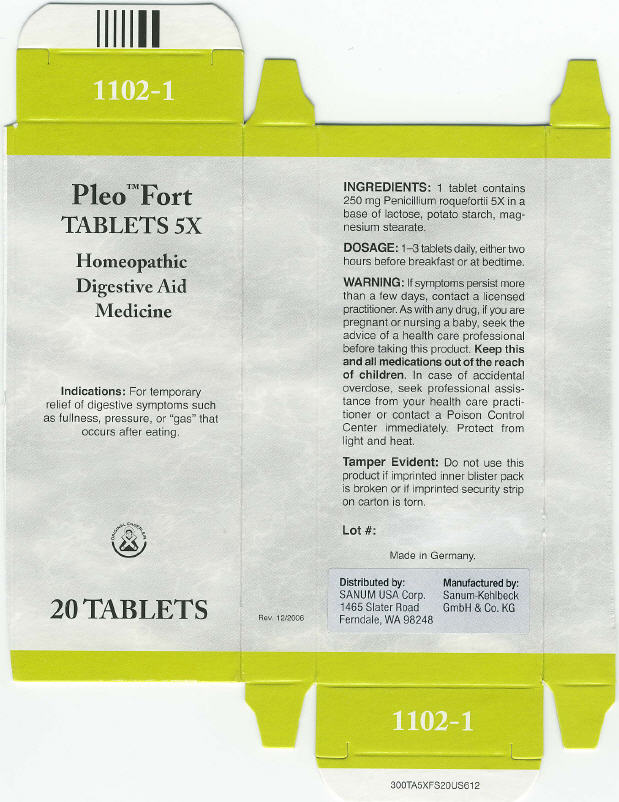 DRUG LABEL: Pleo Fort
NDC: 60681-1102 | Form: TABLET
Manufacturer: Sanum Kehlbeck GmbH & Co. KG
Category: homeopathic | Type: HUMAN OTC DRUG LABEL
Date: 20091012

ACTIVE INGREDIENTS: penicillium roqueforti 5 [HP_X]/1 1
INACTIVE INGREDIENTS: lactose; Starch, Potato; Magnesium Stearate

Pleo™ Fort
TABLETS 5X

Homeopathic Digestive Aid Medicine

20 TABLETS

Indications

For temporary relief of digestive symptoms such as fullness, pressure, or "gas" that occurs after eating.

INGREDIENTS

1 tablet contains 250 mg Penicillium roquefortii 5X in a base of lactose, potato starch, magnesium stearate.

DOSAGE

1–3 tablets daily, either two hours before breakfast or at bedtime.

WARNING

If symptoms persist more than a few days, contact a licensed practitioner. As with any drug, if you are pregnant or nursing a baby, seek the advice of a health care professional before taking this product.

KEEP OUT OF REACH OF CHILDREN

Keep this and all medications out of the reach of children. In case of accidental overdose, seek professional assistance from your health care practitioner or contact a Poison Control Center immediately.

STORAGE AND HANDLING

Protect from light and heat.

Tamper Evident

Do not use this product if imprinted inner blister pack is broken or if imprinted security strip on carton is torn.

Lot #:

Made in Germany.

Distributed by:
SANUM USA Corp.
1465 Slater Road
Ferndale, WA 98248

Manufactured by:
Sanum-Kehlbeck
GmbH & Co. KG

Rev. 12/2006

PRINCIPAL DISPLAY PANEL - 20 Tablets Carton

Pleo™ Fort
TABLETS 5X

Homeopathic
Digestive Aid
Medicine

lndications: For temporary
relief of digestive symptoms such
as fullness, pressure, or "gas" that
occurs after eating.

ORIGINAL ENDERLEIN

20 TABLETS